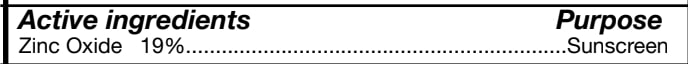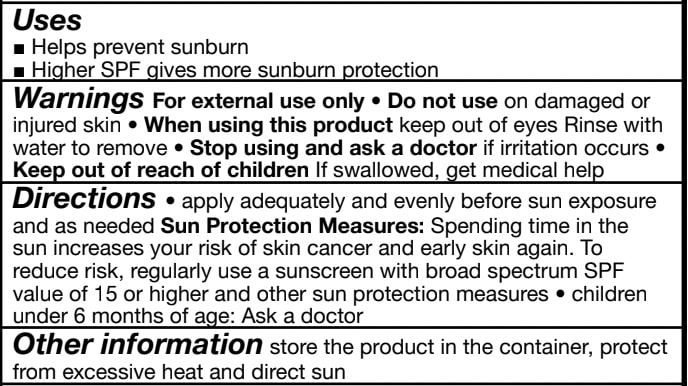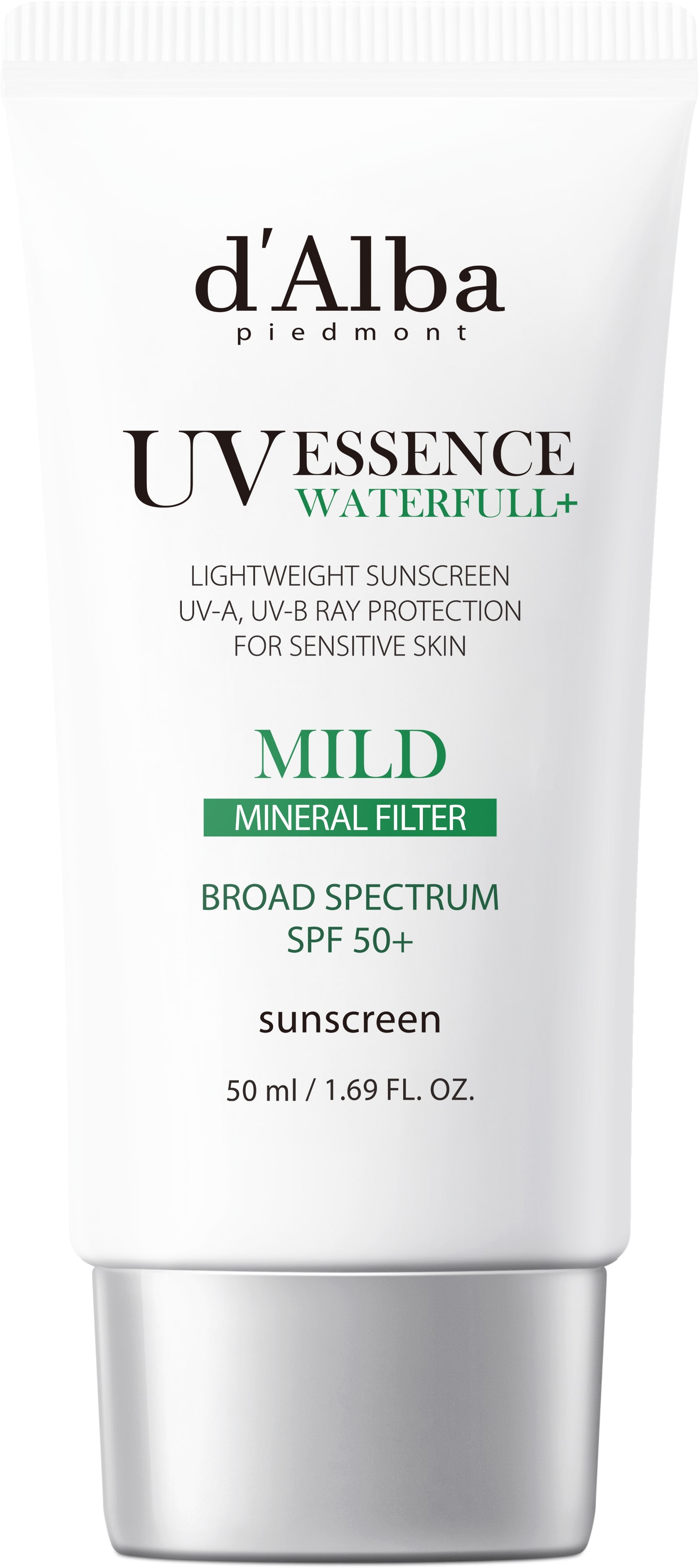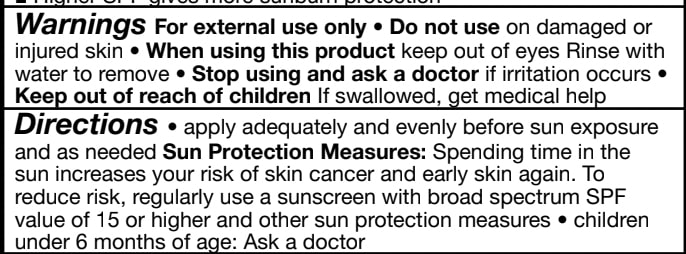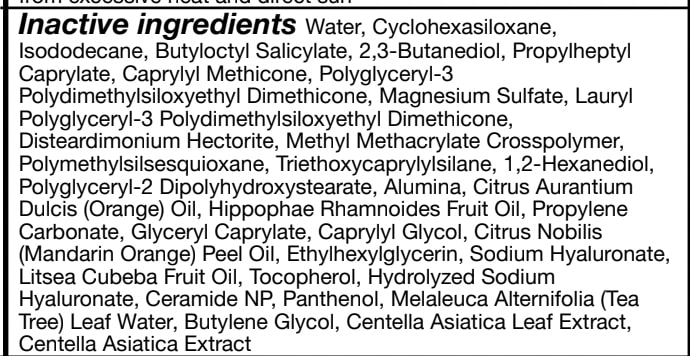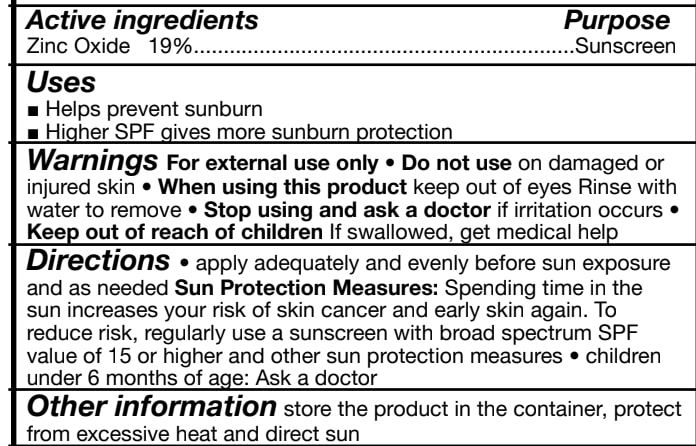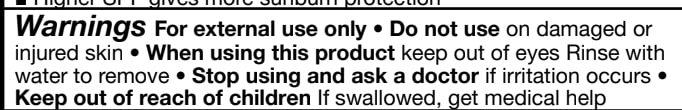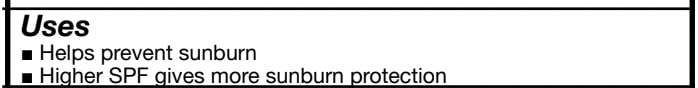 DRUG LABEL: dAlba Vegan Mild Sunscreen
NDC: 84662-030 | Form: CREAM
Manufacturer: ADMTMAX LLC
Category: otc | Type: HUMAN OTC DRUG LABEL
Date: 20250608

ACTIVE INGREDIENTS: ZINC OXIDE 19 mg/50 mL
INACTIVE INGREDIENTS: ISODODECANE

d'Alba Vegan Mild Sunscreen